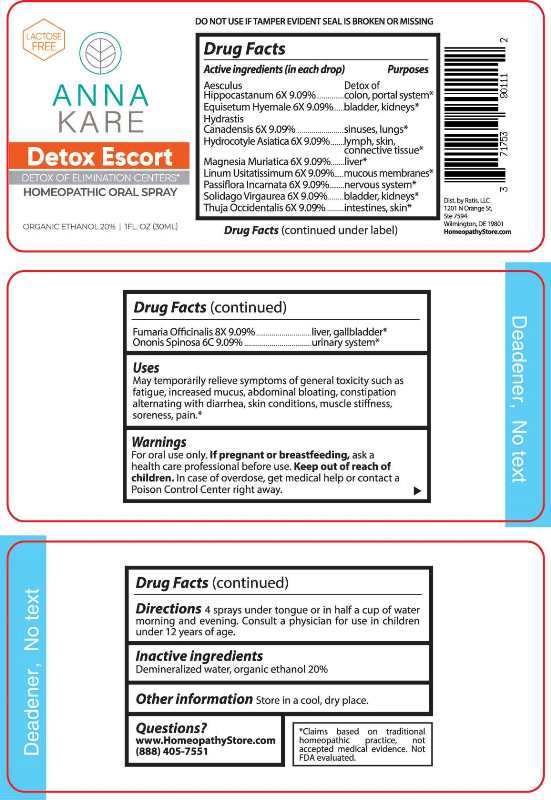 DRUG LABEL: Detox Escort
NDC: 71753-9011 | Form: SPRAY
Manufacturer: Ratis, LLC
Category: homeopathic | Type: HUMAN OTC DRUG LABEL
Date: 20240927

ACTIVE INGREDIENTS: HORSE CHESTNUT 6 [hp_X]/1 mL; EQUISETUM HYEMALE WHOLE 6 [hp_X]/1 mL; GOLDENSEAL 6 [hp_X]/1 mL; CENTELLA ASIATICA WHOLE 6 [hp_X]/1 mL; MAGNESIUM CHLORIDE 6 [hp_X]/1 mL; FLAX SEED 6 [hp_X]/1 mL; PASSIFLORA INCARNATA FLOWERING TOP 6 [hp_X]/1 mL; SOLIDAGO VIRGAUREA FLOWERING TOP 6 [hp_X]/1 mL; THUJA OCCIDENTALIS LEAFY TWIG 6 [hp_X]/1 mL; FUMARIA OFFICINALIS FLOWERING TOP 8 [hp_X]/1 mL; ONONIS SPINOSA WHOLE 6 [hp_C]/1 mL
INACTIVE INGREDIENTS: WATER; ALCOHOL

DRUG FACTS:

ACTIVE INGREDIENTS:

(in each drop) Aesculus Hippocastanum 6X 9.09%, Equisetum Hyemale 6X 9.09%, Hydrastis Canadensis 6X 9.09%, Hydrocotyle Asiatica 6X 9.09%, Magnesia Muriatica 6X 9.09%, Linum Usitatissimum 6X 9.09%, Passiflora Incarnata 6X 9.09%, Solidago Virgaurea 6X 9.09%, Thuja Occidentalis 6X 9.09%, Fumaria Officinalis 8X 9.09%, Ononis Spinosa 6C 9.09%.

PURPOSE:

Aesculus Hippocastanum – Detox of colon, portal system,* Equisetum Hyemale – bladder, kidneys,* Hydrastis Canadensis – sinuses, lungs,* Hydrocotyle Asiatica – lymph, skin, connective tissue,* Magnesia Muriatica - liver,* Linum Usitatissimum – mucous membranes,* Passiflora Incarnata – nervous system,* Solidago Virgaurea – bladder kidneys,* Thuja Occidentalis – intestine, skin,* Fumaria Officinalis – liver, gallbladder,* Ononis Spinosa – urinary system.*

USES:

May temporarily relieve symptoms of general toxicity such as fatigue, increased mucus, abdominal bloating, constipation alternating with diarrhea, skin conditions, muscle stiffness, soreness, pain.*

*Claims based on traditional homeopathic practice, not accepted medical evidence. Not FDA evaluated.

WARNINGS:

For oral use only.

If pregnant or breast-feeding, ask a health care professional before use.

Keep out of reach of children. In case of overdose, get medical help or contact a Poison Control Center right away.

DO NOT USE IF TAMPER EVIDENT SEAL IS BROKEN OR MISSING

KEEP OUT OF REACH OF CHILDREN:

In case of overdose, contact physician or Poison Control Center right away.

DIRECTIONS:

4 sprays under tongue or in half a cup of water morning and evening. Consult a physician for use in children under 12 years of age.

Store in a cool, dry place.

INACTIVE INGREDIENTS:

Demineralized water, organic ethanol 20%

QUESTIONS:

www.HomeopathyStore.com

(888) 405-7551

Dist. by Ratis, LLC,

1201 N Orange St,

Ste 7594

Wilmington, De 19801

PACKAGE LABEL DISPLAY:

LACTOSE FREE

ANNA

KARE

Detox Escort

DETOX OF ELIMINATION CENTERS*

HOMEOPATHIC ORAL SPRAY

1 FL. OZ (30ML)